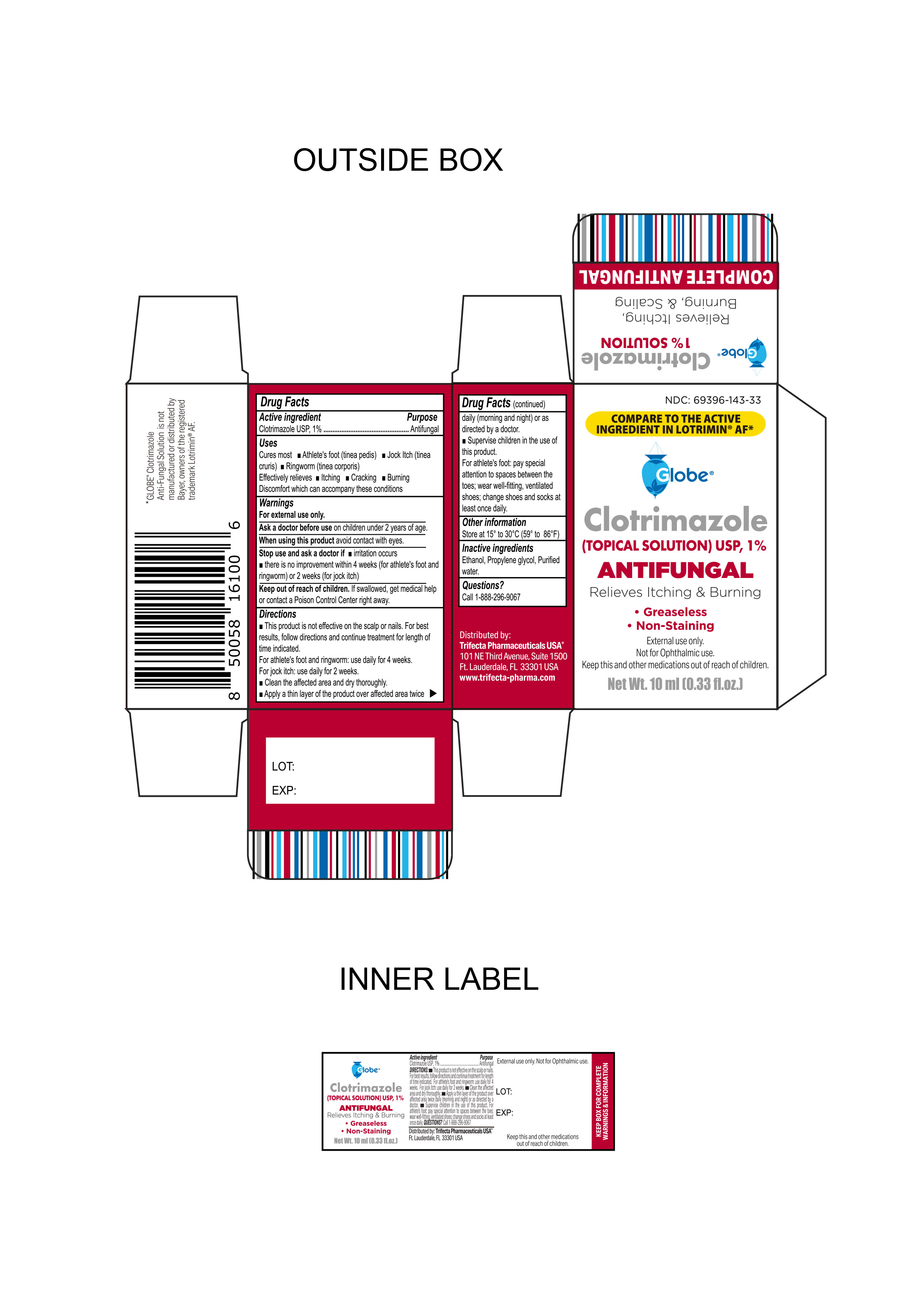 DRUG LABEL: Clotrimazole Antifungal
NDC: 69396-143 | Form: SOLUTION
Manufacturer: Trifecta Pharmaceuticals USA, LLC.
Category: otc | Type: HUMAN OTC DRUG LABEL
Date: 20240219

ACTIVE INGREDIENTS: CLOTRIMAZOLE 10 g/1 L
INACTIVE INGREDIENTS: PROPYLENE GLYCOL; WATER; ALCOHOL

Globe Clotrimazole (Topical Solution) USP 1%

Active Ingredient

Clotrimazole USP, 1.0%

Purpose

Antifungal

Uses

Cures most

- Athlete's foot (tinea pedis)
- Jock Itch (Tinea Cruris)
- Ringwork (Tinea corporis)

Effectively relieves

- Itching
- Cracking
- Burning

Discomfort that can accompany these conditions

Warnings

For External Use Only

Stop use and ask a doctor

- If irritation occurs
- If there is no improvement within 4 weeks (for athlete's foot and ringworm) or 2 weeks (for jock itch)

Ask a doctor before use on children under 2 years of age

When using this product

Avoid Contact with Eyes.

Keep out of the reach of children

If swallowed, get medical help or contact a Poison Control Center immediately

Directions

- Spray over affected area
- If bandaged, let dry first
- Not to be used on children under 12 years of age

Other information

- Store at controlled room temperature 15º-30ºC (59º-86ºF)

Inactive Ingredients

Ethanol, Propylene glycol, purified water

Questions or Comments

Call 1-888-296-9067

Distributed By:

Trifecta Pharmaceuticals USA®

101 NE Third Avenue, Suite 1500

Ft. Lauderdale, FL. 33301 USA

www.trifecta-pharma.com

Globe® Clotrimazole anti-fungal solution is not manufactured or distributed by Bayer, owner of the registered trademark Lotrimin®AF.